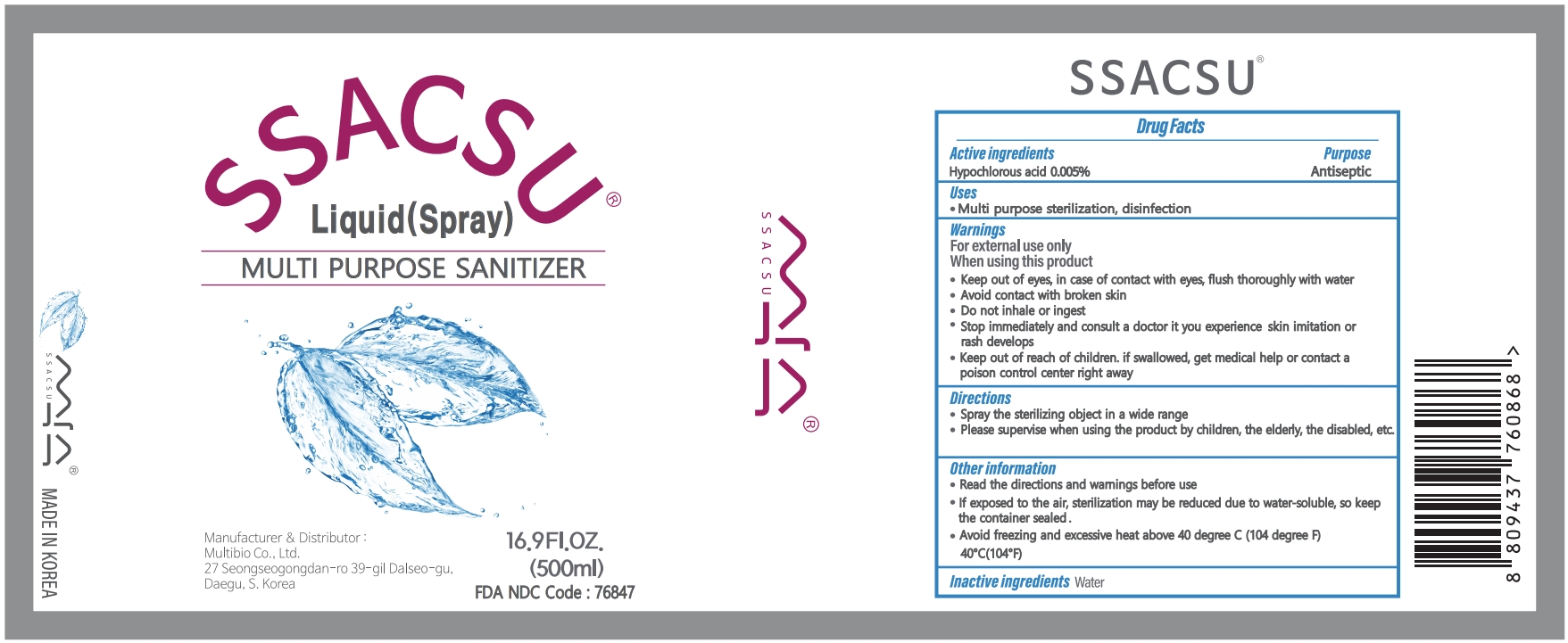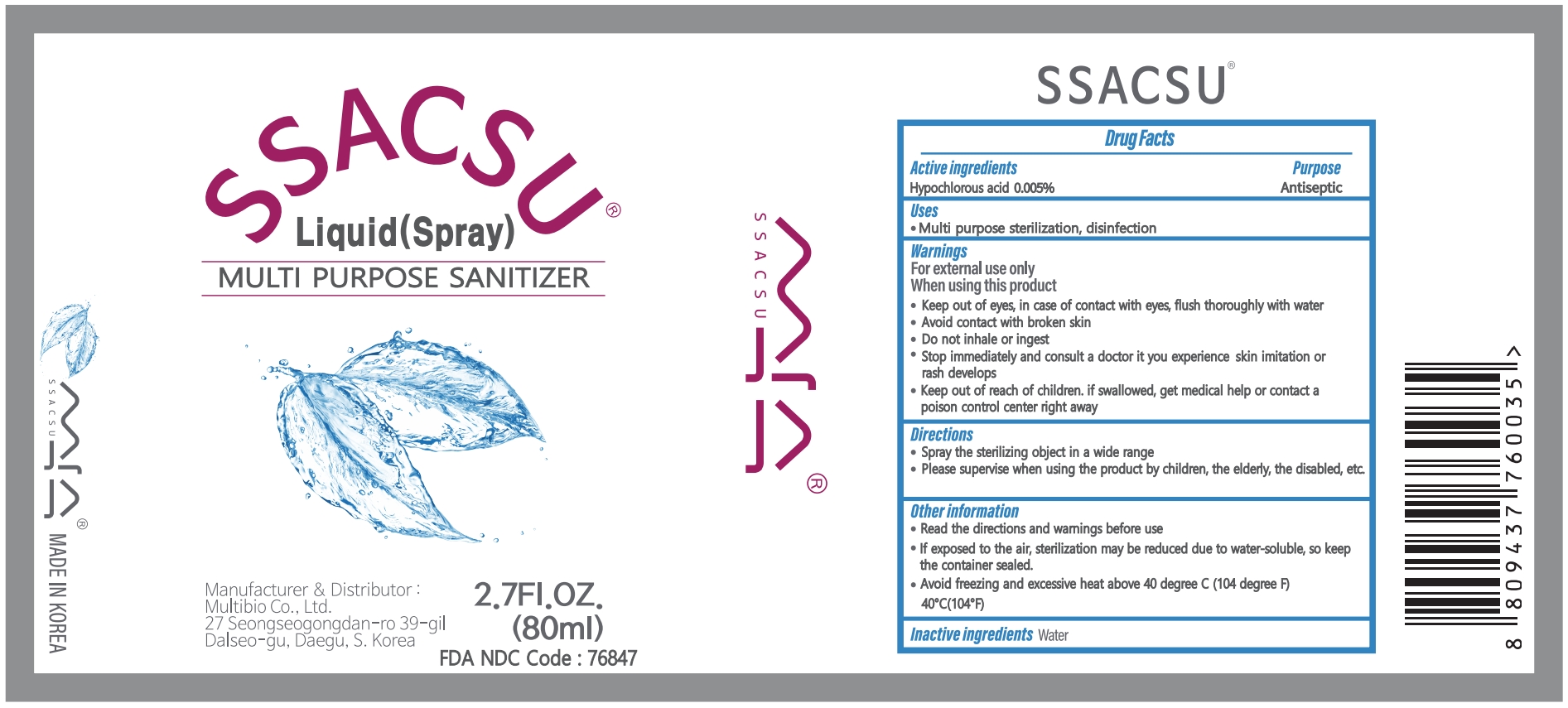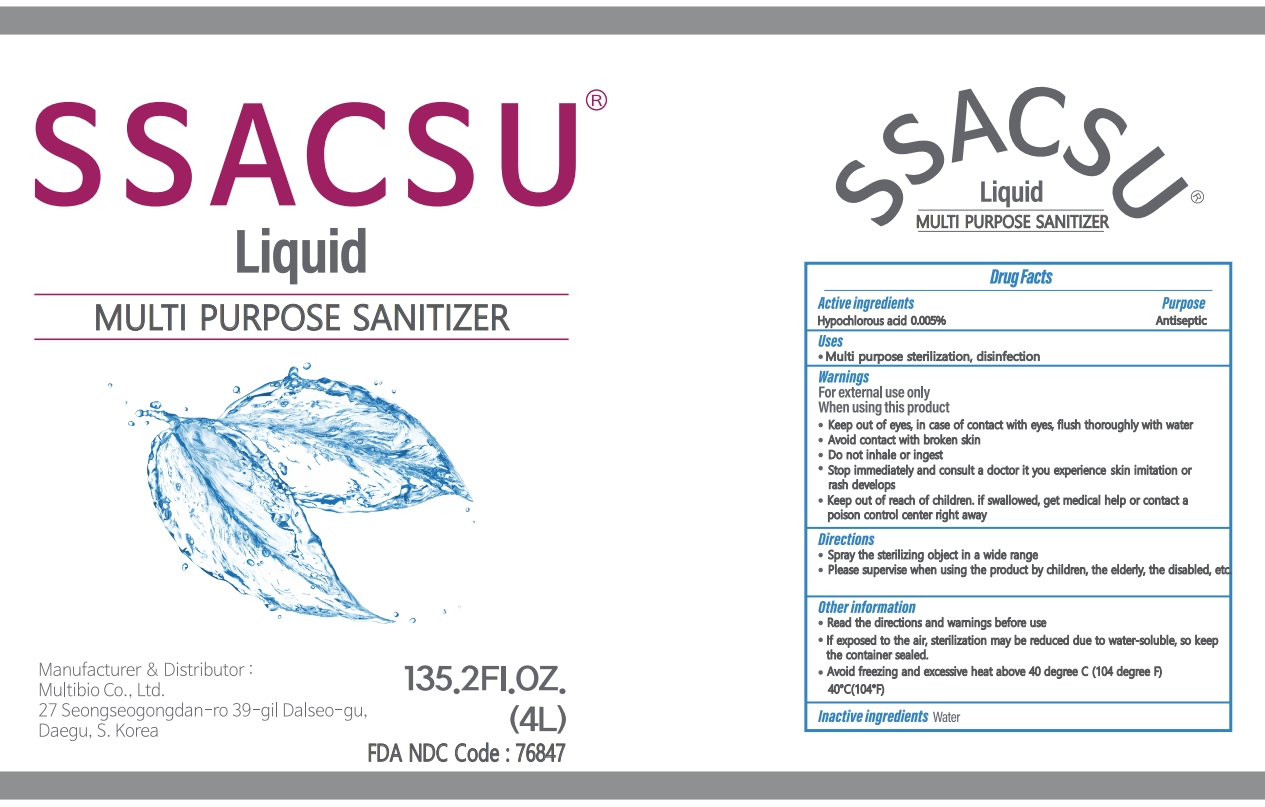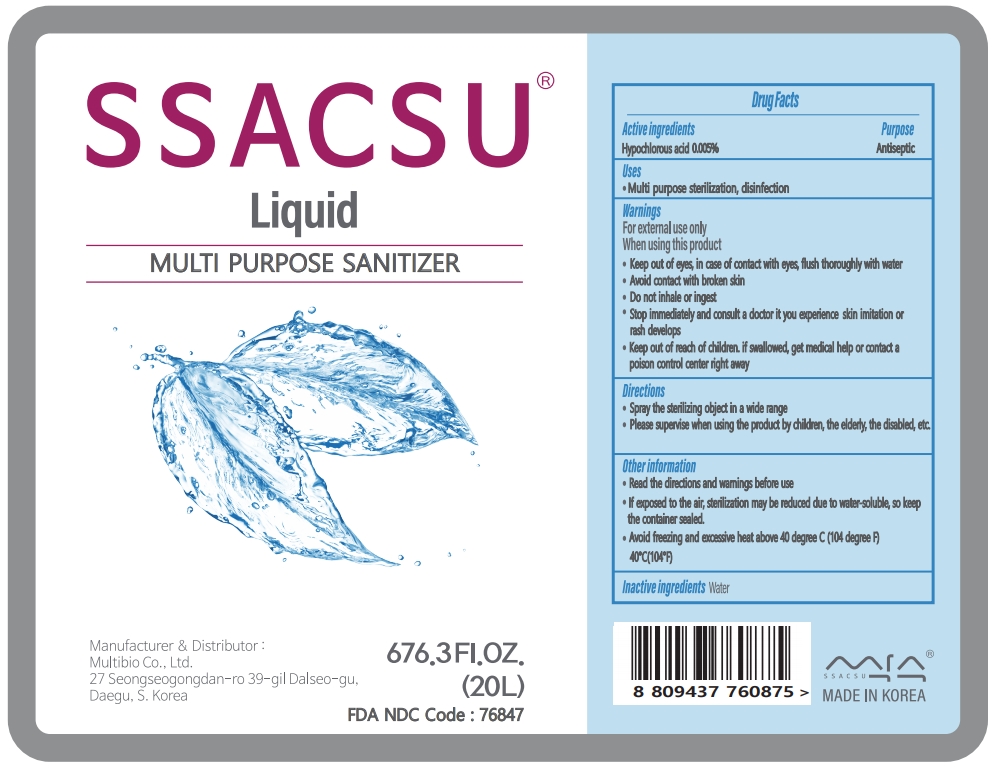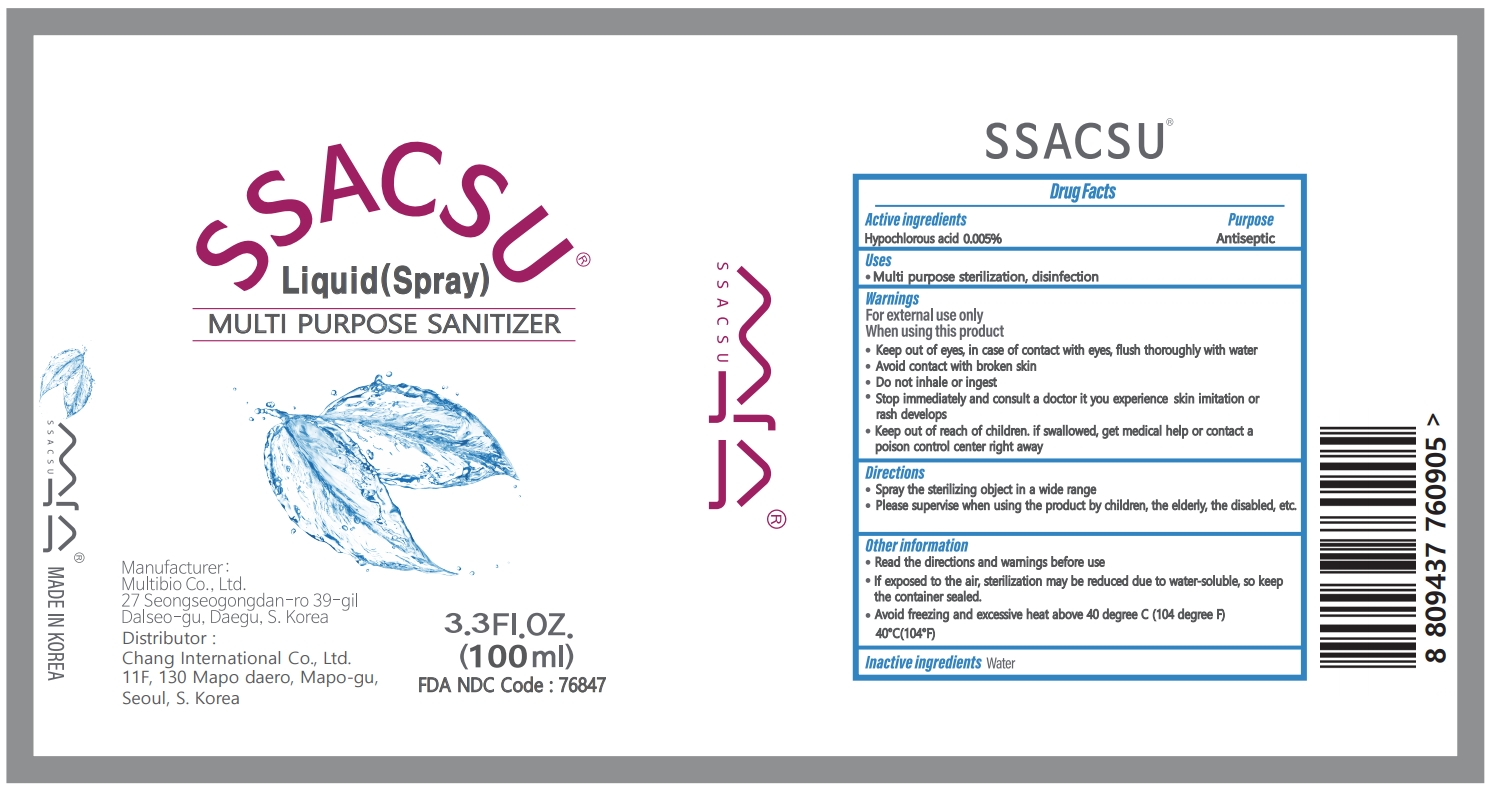 DRUG LABEL: SSACSU
NDC: 76847-201 | Form: LIQUID
Manufacturer: Multibio Co., Ltd
Category: otc | Type: HUMAN OTC DRUG LABEL
Date: 20220218

ACTIVE INGREDIENTS: HYPOCHLOROUS ACID 0.005 g/100 mL
INACTIVE INGREDIENTS: WATER 99.995 mL/100 mL

76847-201

Active ingredients

Hypochlorous Acid 0.005%

Purpose

Antiseptic

Uses

Multi purpose sterilization, disinfection

Warnings

For external use only

When using this product

Keep out of eyes. In case of contact with eyes, flush thoroughly with water.

Avoid contact with broken skin.

Do not inhale or ingest.

When using this product

Stop immediately and consult a doctor it you experience skin imitation or rash develops

When using this product

Keep out of reach of children. If swallowed, get medical help or contact a Poison Control Center right away.

Directions

Spray the sterilizing object in a wide range

Please supervise when using the product by children, the elderly, the disabled, etc.

Other information

Read the directions and warmings before use

If exposed to the air, sterilization may be reduced due to water-soluble, so keep the container sealed.

Avoid freezing and excessive heat above 40 degreee C (104 degree F) 40C(104F)

Inactive ingredients

Water